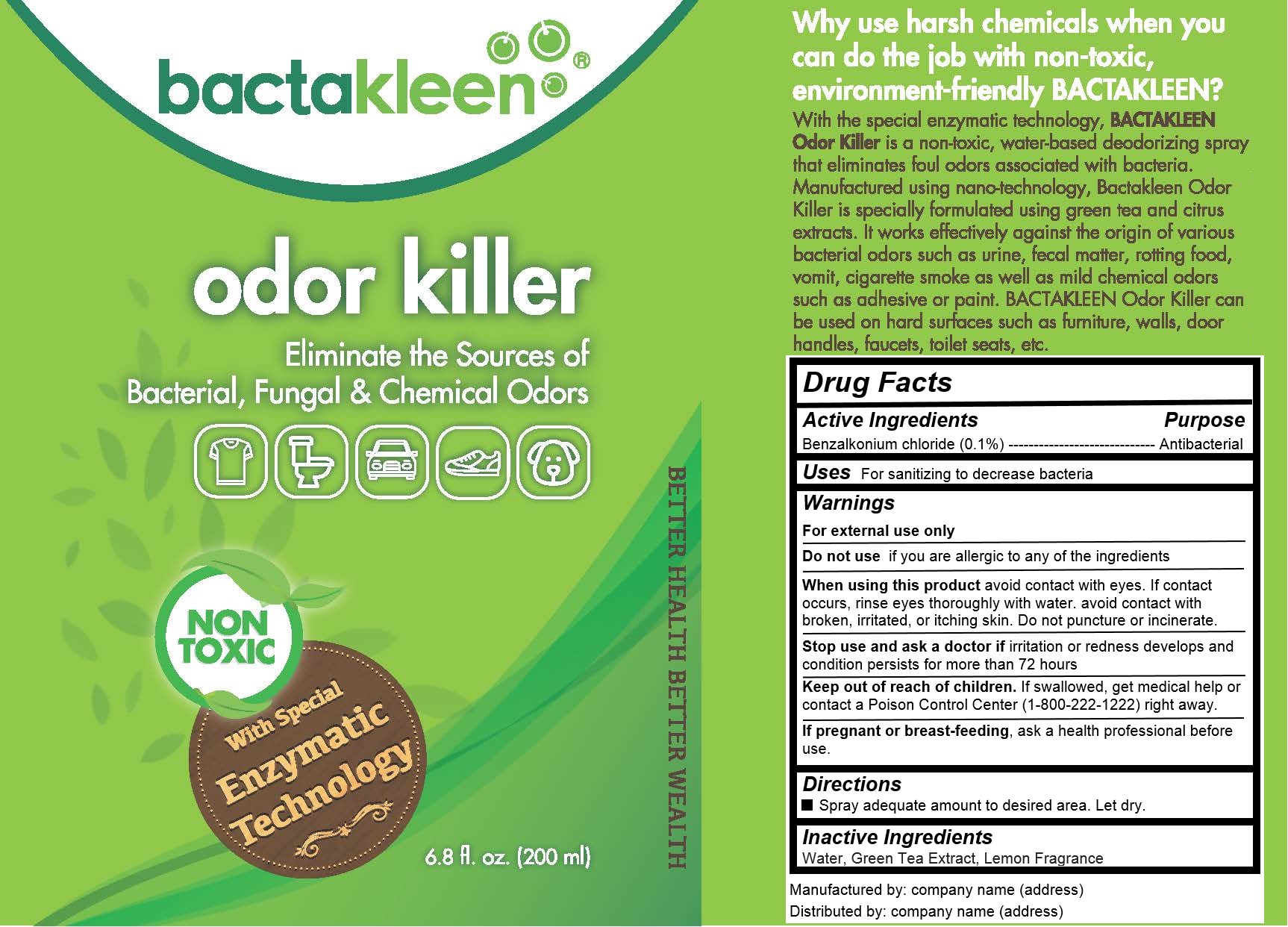 DRUG LABEL: BACTAKLEEN ODOR KILLER
NDC: 73215-104 | Form: LIQUID
Manufacturer: EXCELSIA TECHNOLOGIES SDN BHD
Category: animal | Type: OTC ANIMAL DRUG LABEL
Date: 20200225

ACTIVE INGREDIENTS: benzalkonium chloride 0.2 g/200 mL
INACTIVE INGREDIENTS: WATER

BACTAKLEEN ODOR KILLER